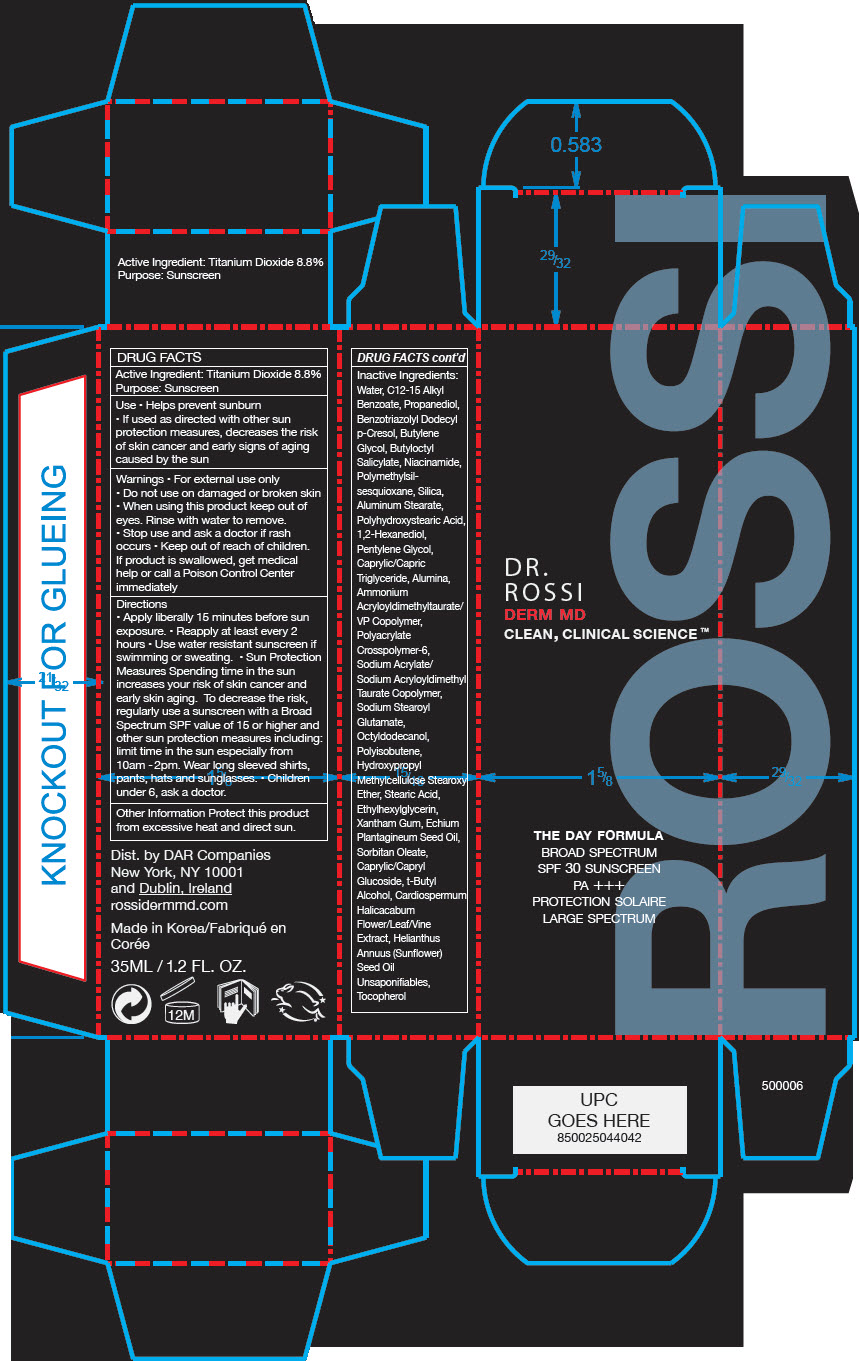 DRUG LABEL: The Day Formula Broad Spectrum SPF 30 Sunscreen
NDC: 80518-123 | Form: CREAM
Manufacturer: Dar Companies, LLC
Category: otc | Type: HUMAN OTC DRUG LABEL
Date: 20230511

ACTIVE INGREDIENTS: Titanium Dioxide 88 mg/1 mL
INACTIVE INGREDIENTS: Water; ALKYL (C12-15) BENZOATE; Propanediol; BENZOTRIAZOLYL DODECYL P-CRESOL; BUTYLENE GLYCOL; BUTYLOCTYL SALICYLATE; NIACINAMIDE; POLYMETHYLSILSESQUIOXANE (4.5 MICRONS); SILICON DIOXIDE; ALUMINUM STEARATE; MEDIUM-CHAIN TRIGLYCERIDES; ALUMINUM OXIDE; AMMONIUM ACRYLOYLDIMETHYLTAURATE/VP COPOLYMER; AMMONIUM ACRYLOYLDIMETHYLTAURATE, DIMETHYLACRYLAMIDE, LAURYL METHACRYLATE AND LAURETH-4 METHACRYLATE COPOLYMER, TRIMETHYLOLPROPANE TRIACRYLATE CROSSLINKED (45000 MPA.S); SODIUM STEAROYL GLUTAMATE; OCTYLDODECANOL; STEARIC ACID; ETHYLHEXYLGLYCERIN; XANTHAN GUM; ECHIUM PLANTAGINEUM SEED OIL; SORBITAN MONOOLEATE; TERT-BUTYL ALCOHOL; CARDIOSPERMUM HALICACABUM FLOWERING TOP; SUNFLOWER OIL UNSAPONIFIABLES; TOCOPHEROL; 1,2-HEXANEDIOL; PENTYLENE GLYCOL

The Day Formula

DRUG FACTS

Active Ingredient

Titanium Dioxide 8.8%

Purpose

Sunscreen

Use

- Helps prevent sunburn
- If used as directed with other sun protection measures, decreases the risk of skin cancer and early signs of aging caused by the sun

Warnings

- For external use only

- Do not use on damaged or broken skin

- When using this product keep out of eyes. Rinse with water to remove.

- Stop use and ask a doctor if rash occurs

- Keep out of reach of children. If product is swallowed, get medical help or call a Poison Control Center immediately

Directions

- Apply liberally 15 minutes before sun exposure.
- Reapply at least every 2 hours
- Use water resistant sunscreen if swimming or sweating.
- Sun Protection Measures Spending time in the sun increases your risk of skin cancer and early skin aging. To decrease the risk, regularly use a sunscreen with a Broad Spectrum SPF value of 15 or higher and other sun protection measures including: limit time in the sun especially from 10am - 2pm. Wear long sleeved shirts, pants, hats and sunglasses.
- Children under 6, ask a doctor.

Other Information

Protect this product from excessive heat and direct sun.

Inactive Ingredients

Water, C12-15 Alkyl Benzoate, Propanediol, Benzotriazolyl Dodecyl p-Cresol, Butylene Glycol, Butyloctyl Salicylate, Niacinamide, Polymethylsilsesquioxane, Silica, Aluminum Stearate, Polyhydroxystearic Acid, 1,2-Hexanediol, Pentylene Glycol, Caprylic/Capric Triglyceride, Alumina, Ammonium Acryloyldimethyltaurate/VP Copolymer, Polyacrylate Crosspolymer-6, Sodium Acrylate/Sodium Acryloyldimethyl Taurate Copolymer, Sodium Stearoyl Glutamate, Octyldodecanol, Polyisobutene, Hydroxypropyl Methylcellulose Stearoxy Ether, Stearic Acid, Ethylhexylglycerin, Xantham Gum, Echium Plantagineum Seed Oil, Sorbitan Oleate, Caprylic/Capryl Glucoside, t-Butyl Alcohol, Cardiospermum Halicacabum Flower/Leaf/Vine Extract, Helianthus Annuus (Sunflower) Seed Oil Unsaponifiables, Tocopherol

Dist. by DAR Companies
New York, NY 10001
and Dublin, Ireland

PRINCIPAL DISPLAY PANEL - 35 ML Bottle Carton

DR.
ROSSI
DERM MD
CLEAN, CLINICAL SCIENCE ™

THE DAY FORMULA
BROAD SPECTRUM
SPF 30 SUNSCREEN
PA +++
PROTECTION SOLAIRE
LARGE SPECTRUM